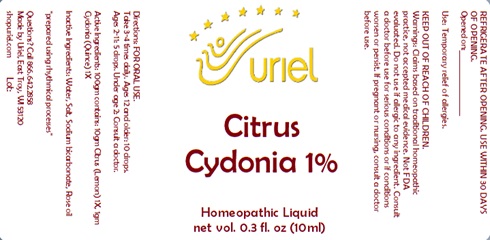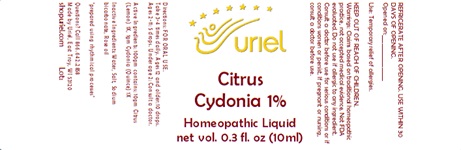 DRUG LABEL: Citrus Cydonia 1%
NDC: 48951-3228 | Form: LIQUID
Manufacturer: Uriel Pharmacy Inc.
Category: homeopathic | Type: HUMAN OTC DRUG LABEL
Date: 20240115

ACTIVE INGREDIENTS: LEMON 1 [hp_X]/1 mL; QUINCE 1 [hp_X]/1 mL
INACTIVE INGREDIENTS: SODIUM BICARBONATE; WATER; SODIUM CHLORIDE; ROSE OIL

Citrus Cydonia 1%

INDICATIONS AND USAGE

Directions: FOR ORAL USE.

DOSAGE AND ADMINISTRATION

Take 3-4 times daily. Ages 12 and older: 10 drops. Ages 2-11: 5 drops. Under age 2: Consult a doctor.

ACTIVE INGREDIENT

Active Ingredients: 100gm contains: 10gm Citrus (Lemon) 1X, 1gm Cydonia (Quince) 1X

INACTIVE INGREDIENT

Inactive Ingredients: Water, Salt, Boric acid, Sodium bicarbonate, Rose oil

"prepared using rhythmical processes"

PURPOSE

Use: Temporary relief of allergies.

KEEP OUT OF REACH OF CHILDREN.

WARNINGS

Warnings: Claims based on traditional homeopathic practice, not accepted medical evidence. Not FDA evaluated. Do not use if allergic to any ingredient. Consult a doctor before use for serious conditions or if conditions worsen or persist. If pregnant or nursing, consult a doctor before use. Do not use if safety seal is broken or missing.

REFRIGERATE AFTER OPENING. USE WITHIN 30 DAYS OF OPENING.
Opened on:_________________

Questions? Call 866.642.2858
Made by Uriel, East Troy, WI 53120
shopuriel.com